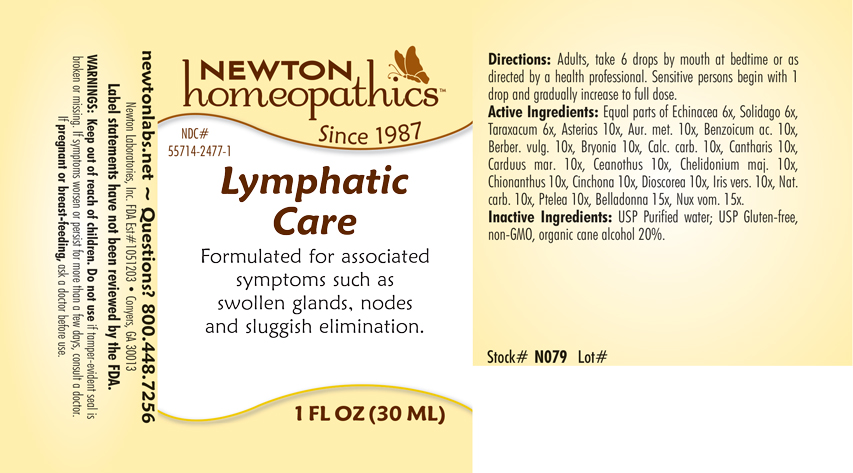 DRUG LABEL: Lymphatic Care
NDC: 55714-2477 | Form: LIQUID
Manufacturer: Newton Laboratories, Inc.
Category: homeopathic | Type: HUMAN OTC DRUG LABEL
Date: 20250207

ACTIVE INGREDIENTS: BERBERIS VULGARIS ROOT BARK 10 [hp_X]/1 mL; LYTTA VESICATORIA 10 [hp_X]/1 mL; OYSTER SHELL CALCIUM CARBONATE, CRUDE 10 [hp_X]/1 mL; ATROPA BELLADONNA 15 [hp_X]/1 mL; BRYONIA ALBA ROOT 10 [hp_X]/1 mL; ASTERIAS RUBENS 10 [hp_X]/1 mL; CHIONANTHUS VIRGINICUS BARK 10 [hp_X]/1 mL; CINCHONA OFFICINALIS BARK 10 [hp_X]/1 mL; DIOSCOREA VILLOSA TUBER 10 [hp_X]/1 mL; IRIS VERSICOLOR ROOT 10 [hp_X]/1 mL; SODIUM CARBONATE 10 [hp_X]/1 mL; STRYCHNOS NUX-VOMICA SEED 15 [hp_X]/1 mL; PTELEA TRIFOLIATA BARK 10 [hp_X]/1 mL; ECHINACEA, UNSPECIFIED 6 [hp_X]/1 mL; TARAXACUM OFFICINALE 6 [hp_X]/1 mL; SOLIDAGO VIRGAUREA FLOWERING TOP 6 [hp_X]/1 mL; GOLD 10 [hp_X]/1 mL; BENZOIC ACID 10 [hp_X]/1 mL; MILK THISTLE 10 [hp_X]/1 mL; CEANOTHUS AMERICANUS LEAF 10 [hp_X]/1 mL; CHELIDONIUM MAJUS 10 [hp_X]/1 mL
INACTIVE INGREDIENTS: WATER; ALCOHOL

Lymphatic 2477L

INDICATIONS & USAGE SECTION

Formulated for associated symptoms such as swollen gland, nodes and sluggish elimination.

DOSAGE & ADMINISTRATION SECTION

Directions: Adults, take 6 drops by mouth at bedtime or as directed by a health professional. Sensitive persons begin with 1 drop and gradually increase to full dose.

OTC - ACTIVE INGREDIENT SECTION

Equal parts of Echinacea 6x, Solidago virgaurea 6x, Taraxacum officinale 6x, Asterias rubens 10x, Aurum metallicum 10x, Benzoicum acidum 10x, Berberis vulgaris 10x, Bryonia 10x, Calcarea carbonica 10x, Cantharis 10x, Carduus marianus 10x, Ceanothus americanus 10x, Chelidonium majus 10x, Chionanthus virginica 10x, Cinchona officinalis 10x, Dioscorea villosa 10x, Iris versicolor 10x, Natrum carbonicum 10x, Ptelea trifoliata 10x, Belladonna 15x, Nux vomica 15x.

OTC - PURPOSE SECTION

Formulated for associated symptoms such as swollen glands, nodes and sluggish elimination.

INACTIVE INGREDIENT SECTION

I nactive Ingredients: USP Purified water; USP Gluten-free, non-GMO, organic cane alcohol 20%.

QUESTIONS SECTION

newtonlabs.net - Questions? 800.448.7256

Newton Laboratories, Inc. FDA Est # 1051203 Conyers, GA 30013

WARNINGS SECTION

WARNINGS: Keep out of reach of children. Do not use if tamper-evident seal is broken or missing. If symptoms worsen or persist for more than a few days, consult a doctor. If pregnant or breast-feeding, ask a doctor before use.

OTC - PREGNANCY OR BREAST FEEDING SECTION

If pregnant or breast-feeding, ask a doctor before use.

OTC - KEEP OUT OF REACH OF CHILDREN

Keep out of reach of children.